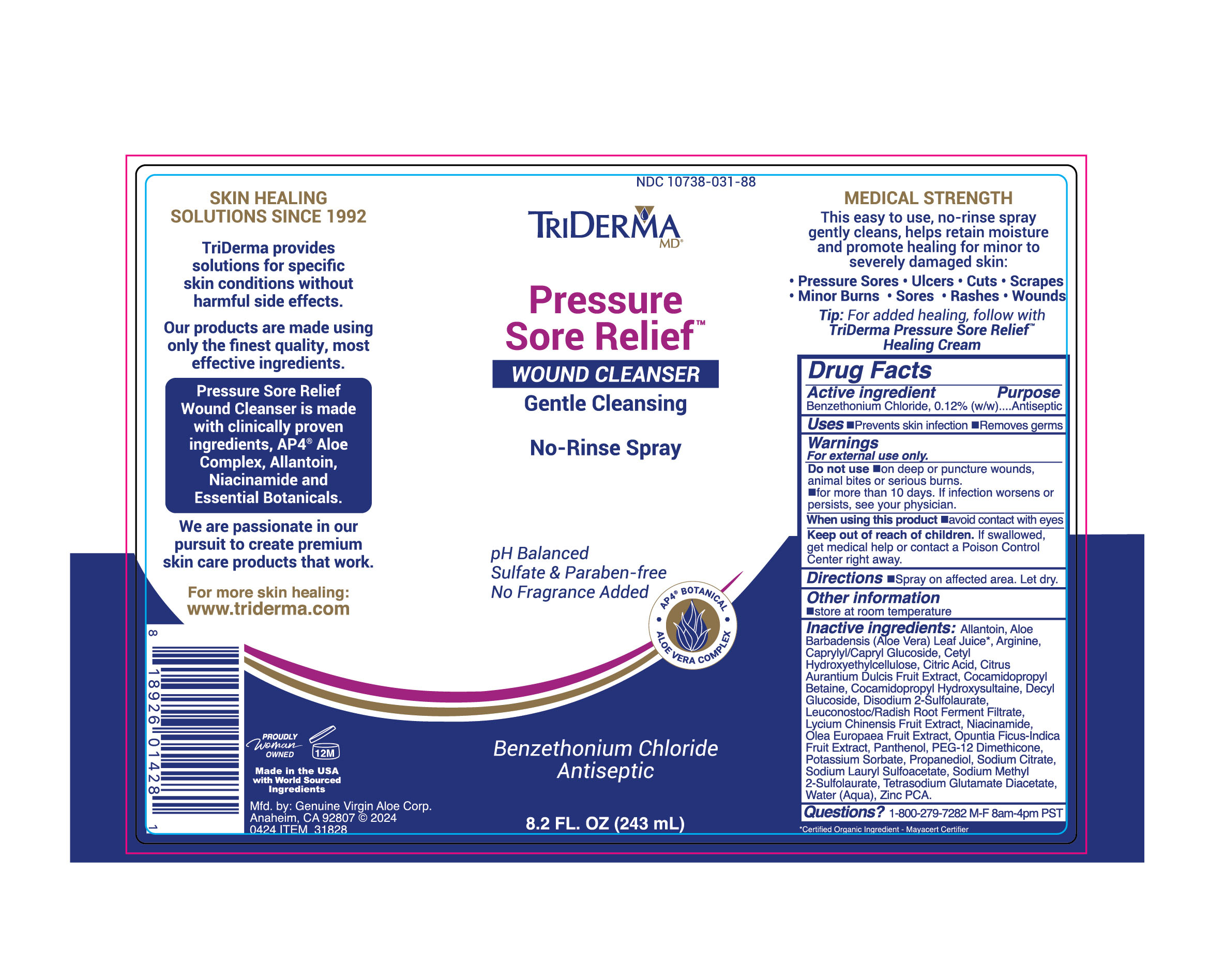 DRUG LABEL: TriDerma Pressure Sore Relief
NDC: 10738-031 | Form: LIQUID
Manufacturer: Genuine Virgin Aloe Corporation
Category: otc | Type: HUMAN OTC DRUG LABEL
Date: 20260128

ACTIVE INGREDIENTS: BENZETHONIUM CHLORIDE 0.0012 g/1 g
INACTIVE INGREDIENTS: ALLANTOIN

Pressure Sore Cleanser

ACTIVE INGREDIENT

Benzethonium Chloride 0.12%

PURPOSE

Antiseptic

INDICATIONS AND USAGE

Prevents skin infection, removes germs

WARNINGS

for external use only

INACTIVE INGREDIENT

allantoin, aloe barbadensis leaf juice, arginine, caprylyl/capryl glucoside, cetyl hydroxyethylcellulose, citric acid, citrus aurantium dulcis fruit extract, cocamidopropyl betaine, cocamidopropyl hydroxysultaine, decyl glucoside, disodium 2-sulfolaurate, leuconostoc/radish root ferment filtrate, lycium chinensis fruit extract, niacinamide, olea europaea fruit extract, opuntia ficus-indica fruit extract, panthenol, peg-12 dimethicone, potassium sorbate, propanediol, sodium citrate, sodium lauryl sulfocaetate, sodium methyul 2-sulfolaurate, tetrasodium glutamate diacetate, water, zinc pca

DOSAGE AND ADMINISTRATION

spray on affected area, let dry

keep out of reach of children. if swallowed, get medical help or contact a poison control center right away.